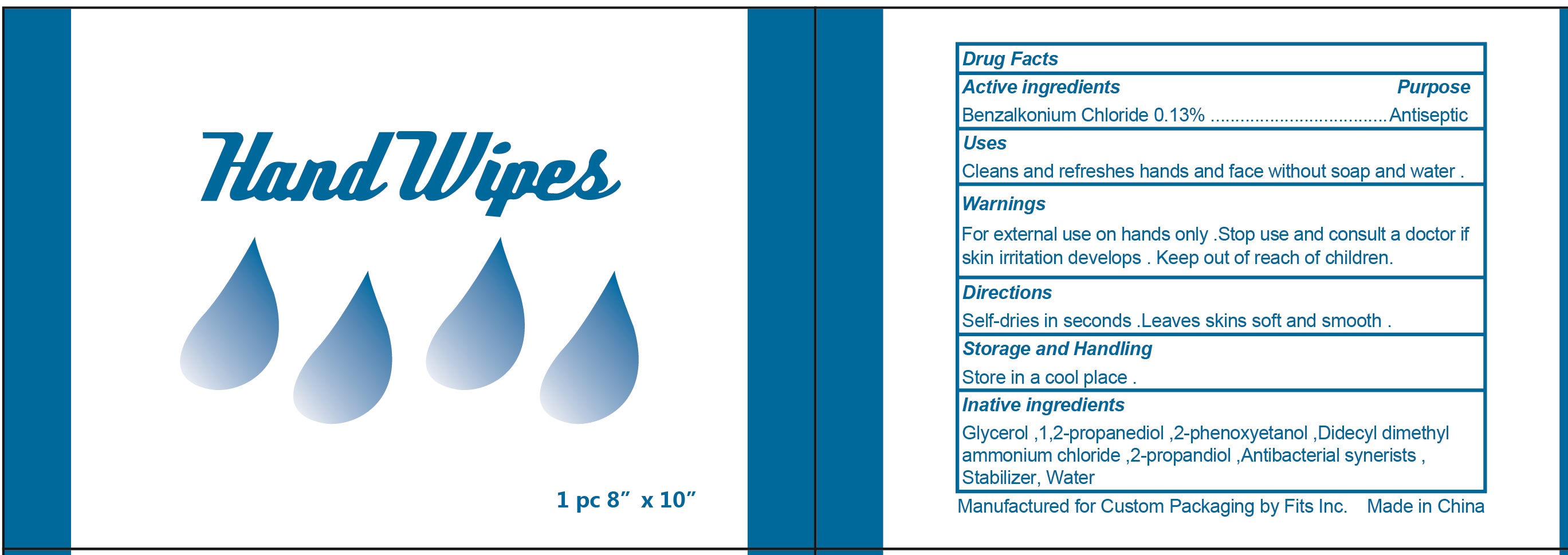 DRUG LABEL: Hand Wipes
NDC: 82447-101 | Form: SWAB
Manufacturer: Meizhou Jubona Technology Co., Ltd.
Category: otc | Type: HUMAN OTC DRUG LABEL
Date: 20211213

ACTIVE INGREDIENTS: benzalkonium chloride 0.13 g/100 g
INACTIVE INGREDIENTS: water; CHLORPHENESIN CARBAMATE

DRUG FACTS

Active Ingredient

Benzalkonium Chloride .......... 0.13 %

Purpose

Antiseptic

Uses:

Cleans and refreshes hands and face without soap and water.

Warnings

DO NOT USE

For external use on hands only. Stop use and ask a doctor if irritation develops.

Store and handling

Store in a cool place.

Keep out of reach of children.

if swallowed get medical help or contact a Poison Control Center right away.

Directions

Self-dries in seconds. Leave skin soft and smooth.

Inactive Ingredients:

Glycerol,1,2-propanediol, 2-phenoxyetanol, Didecyl dimethyl ammonium chloride, 2-propandiol, Antibacterial synerists, Stabilizer, Water